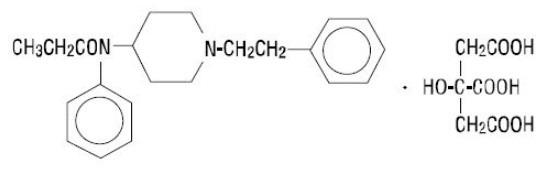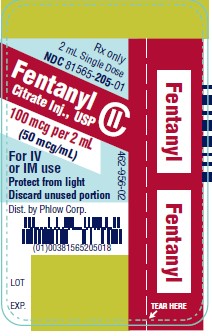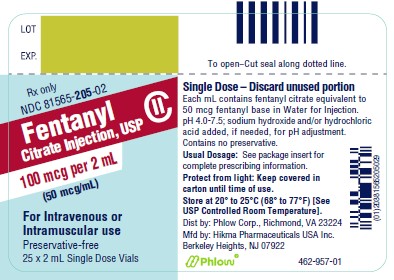 DRUG LABEL: Fentanyl Citrate
NDC: 81565-205 | Form: INJECTION
Manufacturer: Phlow Corp.
Category: prescription | Type: HUMAN PRESCRIPTION DRUG LABEL
Date: 20260227
DEA Schedule: CII

ACTIVE INGREDIENTS: FENTANYL CITRATE 50 ug/1 mL
INACTIVE INGREDIENTS: WATER; SODIUM HYDROXIDE; HYDROCHLORIC ACID

HIGHLIGHTS OF PRESCRIBING INFORMATION

These highlights do not include all the information needed to use FENTANYL CITRATE INJECTION safely and effectively. See full prescribing information for FENTANYL CITRATE INJECTION.
Fentanyl Citrate Injection, for intravenous or intramuscular use, CII
Initial U.S. Approval: 1968

WARNING: SERIOUS AND LIFE-THREATENING RISKSFROM USE OF FENTANYL CITRATE INJECTION

WARNING: SERIOUS AND LIFE-THREATENING RISKS FROM USE OF FENTANYL CITRATE INJECTION
See full prescribing information for complete boxed warning.

- Fentanyl Citrate Injection exposes users to risks of addiction, abuse, and misuse, which can lead to overdose and death. Assess patient’s risk before prescribing and monitor regularly for these behaviors and conditions (5.1)
- Serious, life-threatening, or fatal respiratory depression may occur with use of Fentanyl Citrate Injection, especially during initiation or following a dose increase. To reduce the risk of respiratory depression, proper dosing and titration of Fentanyl Citrate Injection are essential. (5.2)
- Concomitant use of opioids with benzodiazepines or other central nervous system (CNS) depressants, including alcohol, may result in profound sedation, respiratory depression, coma, and death. Reserve concomitant prescribing for use in patients for whom alternative treatment options are inadequate. (5.3, 7)
- Concomitant use with CYP3A4 inhibitors (or discontinuation of CYP3A4 inducers) can result in a fatal overdose of fentanyl. (5.4, 7, 12.3)

RECENT MAJOR CHANGES

Boxed Warning 12/2023

Warnings and Precautions (5.7) 12/2023

1 INDICATIONS AND USAGE

Fentanyl Citrate Injection is indicated for:

- analgesic action of short duration during the anesthetic periods, premedication, induction and maintenance, and in the immediate postoperative period (recovery room) as the need arises.
- use as an opioid analgesic supplement in general or regional anesthesia.
- administration with a neuroleptic as an anesthetic premedication, for the induction of anesthesia and as an adjunct in the maintenance of general and regional anesthesia.
- use as an anesthetic agent with oxygen in selected high-risk patients, such as those undergoing open heart surgery or certain complicated neurological or orthopedic procedures.

2 DOSAGE AND ADMINISTRATION

- Fentanyl Citrate Injection should be administered only by persons specifically trained in the use of intravenous anesthetics and management of the respiratory effects of potent opioids.
- Ensure that an opioid antagonist, resuscitative and intubation equipment, and oxygen are readily available (2.1).
- Individualize dosing based on the factors such as age, body weight, physical status, underlying pathological condition, use of other drugs, type of anesthesia to be used, and the surgical procedure involved. (2.1)
- Initiate treatment in adults with 50 mcg to 100 mcg. (2.2)
- Initiate treatment in children 2 to 12 years of age, with a reduced dose as low as 2 mcg/kg to 3 mcg/kg. (2.2)

3 DOSAGE FORMS AND STRENGTHS

Fentanyl Citrate Injection, equivalent to 50 mcg fentanyl base per mL, is a preservative-free solution, available in a 2 mL single-dose glass vial. (3)

4 CONTRAINDICATIONS

- Hypersensitivity to fentanyl (4)

5 WARNINGS AND PRECAUTIONS

- Risks of Skeletal Muscle Rigidity and Skeletal Muscle Movement: Manage with neuromuscular blocking agent. See full prescribing information for more detail on managing these risks. (5.5)
- Severe Cardiovascular Depression: Monitor during dosage initiation and titration. (5.6)
- Opioid-Induced Hyperalgesia and Allodynia: Opioid-Induced Hyperalgesia (OIH) occurs when an opioid analgesic paradoxically causes an increase in pain, or an increase in sensitivity to pain. If OIH is suspected, carefully consider appropriately decreasing the dose of the current opioid analgesic, or opioid rotation. (5.7)
- Serotonin Syndrome: Potentially life-threatening condition could result from concomitant serotonergic drug administration. Discontinue Fentanyl Citrate Injection if serotonin syndrome is suspected. (5.8)
- Adrenal Insufficiency: If diagnosed, treat with physiologic replacement of corticosteroids, and wean patient off of the opioid. (5.9)
- Risks of Use in Patients with Increased Intracranial Pressure, Brain Tumors, or Head Injury: Monitor for sedation and respiratory depression. (5.10)

6 ADVERSE REACTIONS

Most common serious adverse reactions were respiratory depression, apnea, rigidity, and bradycardia. (6)

To report SUSPECTED ADVERSE REACTIONS, contact Hikma Pharmaceuticals USA Inc. at 1-877-845-0689 or FDA at 1-800-FDA-1088 or www.fda.gov/medwatch.

7 DRUG INTERACTIONS

- Concomitant Use of CNS Depressants: May decrease pulmonary arterial pressure and may cause hypotension. See FPI for management instructions. For post-operative pain, start with the lowest effective dosage and monitor for potentiation of CNS depressant effects. (5.4, 7)
- Mixed Agonist/Antagonist and Partial Agonist Opioid Analgesics: Avoid use with Fentanyl Citrate Injection because they may reduce the analgesic effect of Fentanyl Citrate Injection or precipitate withdrawal symptoms. (7)

8 USE IN SPECIFIC POPULATIONS

- Pregnancy: May cause fetal harm. (8.1)
- Lactation: Infants exposed to Fentanyl Citrate Injection through breast milk should be monitored for excess sedation and respiratory depression. (8.2)
- Geriatric Patients: Titrate slowly and monitor for CNS and respiratory depression. (8.5)

FULL PRESCRIBING INFORMATION

WARNING: SERIOUS AND LIFE-THREATENING RISKSFROM USE OF FENTANYL CITRATE INJECTION

Addiction, Abuse, and Misuse

Because the use of Fentanyl Citrate Injection exposes patients and other users to the risks of opioid addiction, abuse and misuse, which can lead to overdose and death, assess each patient’s risk prior to prescribing and reassess all patients regularly for the development of these behaviors and conditions [see Warnings and Precautions (5.1)].

Life-Threatening Respiratory Depression

Serious, life-threatening, or fatal respiratory depression may occur with use of Fentanyl Citrate Injection, especially during initiation or following a dosage increase. To reduce the risk of respiratory depression, proper dosing and titration of Fentanyl Citrate Injection are essential [see Warnings and Precautions (5.2)].

Risks From Concomitant Use With Benzodiazepines Or Other CNS Depressants

Concomitant use of opioids with benzodiazepines or other central nervous system (CNS)
depressants, including alcohol, may result in profound sedation, respiratory depression, coma, and death. Reserve concomitant prescribing of Fentanyl Citrate Injection and benzodiazepines or other CNS depressants for use in patients for whom alternative treatment options are inadequate [see Warnings and Precautions (5.3), Drug Interactions (7)].

Cytochrome P450 3A4 Interaction

The concomitant use of Fentanyl Citrate Injection with all cytochrome P450 3A4 inhibitors may result in an increase in fentanyl plasma concentrations, which could increase or prolong adverse reactions and may cause potentially fatal respiratory depression. In addition, discontinuation of a concomitantly used cytochrome P450 3A4 inducer may result in an increase in fentanyl plasma concentration. Monitor patients receiving Fentanyl Citrate Injection and any CYP3A4 inhibitor or inducer [see Warnings and Precautions (5.4), Drug Interactions (7), Clinical Pharmacology (12.3)]

1 INDICATIONS AND USAGE

Fentanyl Citrate Injection is indicated for:

- analgesic action of short duration during the anesthetic periods, premedication, induction and maintenance, and in the immediate postoperative period (recovery room) as the need arises.
- use as a narcotic analgesic supplement in general or regional anesthesia.
- administration with a neuroleptic as an anesthetic premedication, for the induction of anesthesia and as an adjunct in the maintenance of general and regional anesthesia.
- use as an anesthetic agent with oxygen in selected high-risk patients, such as those undergoing open heart surgery or certain complicated neurological or orthopedic procedures.

2 DOSAGE AND ADMINISTRATION

2.1 Important Dosage and Administration Instructions

Fentanyl Citrate Injection should be administered only by persons specifically trained in the use of intravenous anesthetics and management of the respiratory effects of potent opioids.

- Ensure that an opioid antagonist, resuscitative and intubation equipment, and oxygen are readily available.
- Individualize dosage based on factors such as age, body weight, physical status, underlying pathological condition, use of other drugs, type of anesthesia to be used, and the surgical procedure involved.
- Monitor vital signs routinely.

As with other potent opioids, the respiratory depressant effect of fentanyl may persist longer than the measured analgesic effect. The total dose of all opioid agonists administered should be considered by the practitioner before ordering opioid analgesics during recovery from anesthesia.

If Fentanyl Citrate Injection is administered with a CNS depressant, become familiar with the properties of each drug, particularly each product’s duration of action. In addition, when such a combination is used, fluids and other countermeasures to manage hypotension should be available [see Warnings and Precautions (5.4)].
Inspect parenteral drug products visually for particulate matter and discoloration prior to administration, whenever solution and container permit.

2.2 Dosage

Premedication in Adults

50 mcg to 100 mcg may be administered intramuscularly 30 to 60 minutes prior to surgery.

Adjunct to General Anesthesia

See Dosage Range Charts below.

Table 1: Dosage Range Chart

Total Dosage (expressed as fentanyl base)

Low Dose—2 mcg/kg
For use in minor, but painful, surgical procedures.
May also provide some pain relief in the immediate postoperative period.

Moderate Dose—2 mcg/kg to 20 mcg/kg
For use in more major surgical procedures, in addition to adequate analgesia, may abolish some of the stress response.
Expect respiratory depression requiring artificial ventilation during anesthesia and careful observation of ventilation postoperatively is essential.

High dose—20 mcg/kg to 50 mcg/kg
For open heart surgery and certain more complicated neurosurgical and orthopedic procedures where surgery is more prolonged, and the stress response to surgery would be detrimental to the well-being of the patient.
In conjunction with nitrous oxide/oxygen has been shown to attenuate the stress response as defined by increased levels of circulating growth hormone, catecholamine, ADH and prolactin.
Expect the need of postoperative ventilation and observation due to extended post-operative respiratory depression.

Maintenance Dose (expressed as fentanyl base)

Low Dose—2 mcg/kg
Additional dosages infrequently needed in these minor procedures.

Moderate Dose—2 mcg/kg to 20 mcg/kg
25 mcg to 100 mcg
Administer intravenously or intramuscularly as needed when movement and/or changes in vital signs indicate surgical stress or lightening of analgesia.

High Dose—20 mcg/kg to 50 mcg/kg
Maintenance dosage [ranging from 25 mcg to one half the initial loading dose] as needed based on vital signs indicative of stress and lightening of analgesia.
Individualize the dosage especially if the anticipated remaining operative time is short.

Adjunct to Regional Anesthesia

50 mcg to 100 mcg may be administered intramuscularly or slowly intravenously, over one to two minutes, when additional analgesia is required.

Postoperatively (recovery room)

50 mcg to 100 mcg may be administered intramuscularly for the control of pain, tachypnea and emergence delirium. The dose may be repeated in one to two hours as needed.

For Induction and Maintenance in Children 2 to 12 Years of Age

A reduced dose as low as 2 mcg/kg to 3 mcg/kg is recommended.

As a General Anesthetic

As a technique to attenuate the responses to surgical stress without the use of additional anesthetic agents, doses of 50 mcg/kg to 100 mcg/kg may be administered with oxygen and a muscle relaxant. In certain cases, doses up to 150 mcg/kg may be necessary to produce this anesthetic effect. It has been used for open heart surgery and certain other major surgical procedures in patients for whom protection of the myocardium from excess oxygen demand is particularly indicated, and for certain complicated neurological and orthopedic procedures.

3 DOSAGE FORMS AND STRENGTHS

Single-Dose Vial:

Fentanyl Citrate Injection, USP, equivalent to 50 mcg fentanyl base per mL, is a preservative-free solution, available in a 2 mL single-dose glass vial.

4 CONTRAINDICATIONS

Fentanyl Citrate Injection is contraindicated in patients with:

- Hypersensitivity to fentanyl (e.g., anaphylaxis) [See Adverse Reactions (6)]

5 WARNINGS AND PRECAUTIONS

5.1 Addiction, Abuse, and Misuse

Fentanyl Citrate Injection contains fentanyl, a Schedule II controlled substance. As an opioid, Fentanyl Citrate Injection exposes users to the risks of addiction, abuse, and misuse [see Drug Abuse and Dependence (9)].

Opioid are sought for nonmedical use and are subject to diversion from legitimate prescribed use. Consider these risks when handling Fentanyl Citrate Injection. Strategies to reduce these risks include proper product storage and control practices for a C-II drug. Contact local state professional licensing board or state-controlled substances authority for information on how to prevent and detect abuse or diversion of this product.

5.2 Life-Threatening Respiratory Depression

Serious, life-threatening, or fatal respiratory depression has been reported with the use of opioids, even when used as recommended. Respiratory depression, if not immediately recognized and treated, may lead to respiratory arrest and death. Adequate facilities should be available for postoperative monitoring and ventilation of patients administered anesthetic doses of Fentanyl Citrate Injection. It is essential that these facilities be fully equipped to handle all degrees of respiratory depression. Management of respiratory depression may include close observation, supportive measures, and use of opioid antagonists, depending on the patient’s clinical status [see Overdosage (10)]. Carbon dioxide (CO2) retention from opioid-induced respiratory depression can exacerbate the sedating effects of opioids.

To reduce the risk of respiratory depression, proper dosing and titration of Fentanyl Citrate Injection are essential. As with other potent opioids, the respiratory depressant effect of Fentanyl Citrate Injection may persist longer than the measured analgesic effect. The total dose of all opioid agonists administered should be considered by the practitioner before ordering opioid analgesics during recovery from anesthesia.

Certain forms of conduction anesthesia, such as spinal anesthesia and some peridural anesthetics can alter respiration by blocking intercostal nerves. Through other mechanisms [see Clinical Pharmacology (12.2)] Fentanyl Citrate Injection can also alter respiration. Therefore, when Fentanyl Citrate Injection is used to supplement these forms of anesthesia, the anesthetist should be familiar with the physiological alterations involved and be prepared to manage them in the patients selected for these forms of anesthesia.

Patients with significant chronic obstructive pulmonary disease or cor pulmonale, and those with a substantially decreased respiratory reserve, hypoxia, hypercapnia, or pre-existing respiratory depression are at increased risk of decreased respiratory drive including apnea, even at recommended dosages of Fentanyl Citrate Injection. Elderly, cachectic, or debilitated patients may have altered pharmacokinetics or altered clearance compared to younger, healthier patients resulting in greater risk for respiratory depression.

Monitor such patients closely including vital signs, particularly when initiating and titrating Fentanyl Citrate Injection and when Fentanyl Citrate Injection is given concomitantly with other drugs that depress respiration. To reduce the risk of respiratory depression, proper dosing and titration of Fentanyl Citrate Injection are essential [see Dosage and Administration (2.1)].

Opioids can cause sleep-related breathing disorders including central sleep apnea (CSA) and sleep-related hypoxemia. Opioid use increases the risk of CSA in a dose-dependent fashion. In patients who present with CSA, consider decreasing the opioid dosage using best practices for opioid taper [see Dosage and Administration (2.1)].

5.3 Risks from Concomitant Use with Benzodiazepines or Other CNS Depressants

When benzodiazepines or other CNS depressants are used with Fentanyl Citrate Injection, pulmonary arterial pressure may be decreased. This fact should be considered by those who conduct diagnostic and surgical procedures where interpretation of pulmonary arterial pressure measurements might determine final management of the patient. When high dose or anesthetic dosages of Fentanyl Citrate Injection are employed, even relatively small dosages of diazepam may cause cardiovascular depression.

When Fentanyl Citrate Injection is used with CNS depressants, hypotension can occur. If it occurs, consider the possibility of hypovolemia and manage with appropriate parenteral fluid therapy. When operative conditions permit, consider repositioning the patient to improve venous return to the heart. Exercise care in moving and repositioning of patients because of the possibility of orthostatic hypotension. If volume expansion with fluids plus other countermeasures do not correct hypotension, consider administration of pressor agents other than epinephrine.

Epinephrine may paradoxically decrease blood pressure in patients treated with a neuroleptic that blocks alpha adrenergic activity.

Profound sedation, respiratory depression, coma, and death may result from the concomitant use of Fentanyl Citrate Injection with benzodiazepines and/or other CNS depressants, including alcohol (e.g., nonbenzodiazepine sedatives/hypnotics, anxiolytics, tranquilizers, muscle relaxants, general anesthetics, antipsychotics, other opioids).

Observational studies have demonstrated that concomitant use of opioid analgesics and benzodiazepines increases the risk of drug-related mortality compared to use of opioid analgesics alone. Because of similar pharmacological properties, it is reasonable to expect similar risk with the concomitant use of other CNS depressant drugs with opioid analgesics [see Drug Interactions (7)].

If the decision is made to manage postoperative pain with Fentanyl Citrate Injection concomitantly with a benzodiazepine or other CNS depressant, start dosing with the lowest effective dosage and titrate based on clinical response. Monitor patients closely for signs and symptoms of respiratory depression, sedation, and hypotension. Fluids or other measures to counter hypotension should be available [see Drug Interactions (7)].

5.4 Risks of Concomitant Use or Discontinuation of Cytochrome P450 3A4 Inhibitors and Inducers

Concomitant use of Fentanyl Citrate Injection with a CYP3A4 inhibitor, such as macrolide antibiotics (e.g., erythromycin), azole-antifungal agents (e.g., ketoconazole), and protease inhibitors (e.g., ritonavir), may increase plasma concentrations of fentanyl and prolong opioid adverse reactions, which may exacerbate respiratory depression [see Warnings and Precautions (5.2)], particularly when an inhibitor is added after a stable dose of Fentanyl Citrate Injection is achieved. Similarly, discontinuation of a CYP3A4 inducer, such as rifampin, carbamazepine, and phenytoin, in Fentanyl Citrate Injection-treated patients may increase fentanyl plasma concentrations and prolong opioid adverse reactions. When using Fentanyl Citrate Injection with CYP3A4 inhibitors or discontinuing CYP3A4 inducers in Fentanyl Citrate Injection-treated patients, monitor patients closely at frequent intervals and consider dosage reduction of Fentanyl Citrate Injection [see Dosage and Administration (2.1), Drug Interactions (7)].

Concomitant use of Fentanyl Citrate Injection with CYP3A4 inducers or discontinuation of a CYP3A4 inhibitor, could result in lower than expected fentanyl plasma concentrations, decreased efficacy, or, possibly, lead to a withdrawal syndrome in a patient who had developed physical dependence to fentanyl. When using Fentanyl Citrate Injection with CYP3A4 inducers, or discontinuation of a CYP3A4 inhibitor, monitor patients closely at frequent intervals and consider increasing the Fentanyl Citrate Injection dosage [see Dosage and Administration (2.1), Drug Interactions (7)].

5.5 Risks of Muscle Rigidity and Skeletal Muscle Movement

Fentanyl Citrate Injection may cause muscle rigidity, particularly involving the muscles of respiration. The incidence and severity of muscle rigidity is dose related. These effects are related to the dose and speed of injection. Skeletal muscle rigidity also has been reported to occur or recur infrequently in the extended postoperative period usually following high dose administration. In addition, skeletal muscle movements of various groups in the extremities, neck, and external eye have been reported during induction of anesthesia with Fentanyl Citrate Injection; these reported movements have, on rare occasions, been strong enough to pose patient management problems.

These effects are related to the dose and speed of injection and its incidence can be reduced by: 1) administration of up to 1/4 of the full paralyzing dose of a non-depolarizing neuromuscular blocking agent just prior to administration of Fentanyl Citrate Injection; 2) administration of a full paralyzing dose of a neuromuscular blocking agent following loss of eyelash reflex when Fentanyl Citrate Injection is used in anesthetic doses titrated by slow intravenous infusion; or, 3) simultaneous administration of Fentanyl Citrate Injection and a full paralyzing dose of a neuromuscular blocking agent when Fentanyl Citrate Injection is used in rapidly administered anesthetic dosages.
The neuromuscular blocking agent used should be compatible with the patient’s cardiovascular status.

5.6 Severe Cardiovascular Depression

Fentanyl Citrate Injection may cause severe bradycardia, severe hypotension including orthostatic hypotension, and syncope. There is increased risk in patients whose ability to maintain blood pressure has already been compromised by a reduced blood volume or concurrent administration of certain CNS depressant drugs (e.g., phenothiazines or general anesthetics) [see Drug Interactions (7)]. In patients with circulatory shock, Fentanyl Citrate Injection may cause vasodilation that can further reduce cardiac output and blood pressure. Monitor these patients for signs of hypotension after initiating or titrating the dosage of Fentanyl Citrate Injection.

5.7 Opioid-Induced Hyperalgesia and Allodynia

Opioid-Induced Hyperalgesia (OIH) occurs when an opioid analgesic paradoxically causes an increase in pain, or an increase in sensitivity to pain. This condition differs from tolerance, which is the need for increasing doses of opioids to maintain a defined effect [see Dependence (9.3)]. Symptoms of OIH include (but may not be limited to) increased levels of pain upon opioid dosage increase, decreased levels of pain upon opioid dosage decrease, or pain from ordinarily non-painful stimuli (allodynia). These symptoms may suggest OIH only if there is no evidence of underlying disease progression, opioid tolerance, opioid withdrawal, or addictive behavior.

Cases of OIH have been reported, both with short-term and longer-term use of opioid analgesics. Though the mechanism of OIH is not fully understood, multiple biochemical pathways have been implicated. Medical literature suggests a strong biological plausibility between opioid analgesics and OIH and allodynia. If a patient is suspected to be experiencing OIH, carefully consider appropriately decreasing the dose of the current opioid analgesic or opioid rotation (safely switching the patient to a different opioid moiety) [see Dosage and Administration (2)].

5.8 Serotonin Syndrome with Concomitant Use of Serotonergic Drugs

Cases of serotonin syndrome, a potentially life-threatening condition, have been reported during concomitant use of fentanyl with serotonergic drugs. Serotonergic drugs include selective serotonin reuptake inhibitors (SSRIs), serotonin and norepinephrine reuptake inhibitors (SNRIs), tricyclic antidepressants (TCAs), triptans, 5-HT3 receptor antagonists, drugs that affect the serotonergic neurotransmitter system (e.g., mirtazapine, trazadone, tramadol), certain muscle relaxants (i.e., cyclobenzaprine, metaxalone), and drugs that impair metabolism of serotonin (including MAO inhibitors, both those intended to treat psychiatric disorders and also others, such as linezolid and intravenous methylene blue) [see Drug Interactions (7)]. This may occur within the recommended dosage range.

Serotonin syndrome symptoms may include mental status changes (e.g., agitation, hallucinations, coma), autonomic instability (e.g., tachycardia, labile blood pressure, hyperthermia), neuromuscular aberrations (e.g., hyperreflexia, incoordination, rigidity), and/or gastrointestinal symptoms (e.g., nausea, vomiting, diarrhea) and can be fatal. The onset of symptoms generally occurs within several hours to a few days of concomitant use but may occur later than that. Discontinue Fentanyl Citrate Injection if serotonin syndrome is suspected.

5.9 Adrenal Insufficiency

Cases of adrenal insufficiency have been reported with opioid use, more often following greater than one month of use. Presentation of adrenal insufficiency may include non-specific symptoms and signs including nausea, vomiting, anorexia, fatigue, weakness, dizziness, and low blood pressure. If adrenal insufficiency is suspected, confirm the diagnosis with diagnostic testing as soon as possible. If adrenal insufficiency is diagnosed, treat with physiologic replacement doses of corticosteroids. Wean the patient off of the opioid to allow adrenal function to recover and continue corticosteroid treatment until adrenal function recovers. Other opioids may be tried as some cases reported use of a different opioid without recurrence of adrenal insufficiency. The information available does not identify any particular opioids as being more likely to be associated with adrenal insufficiency.

5.10 Risks of Use in Patients with Increased Intracranial Pressure, Brain Tumors, or Head Injury

In patients who may be susceptible to the intracranial effects of CO2 retention (e.g., those with evidence of increased intracranial pressure or brain tumors), Fentanyl Citrate Injection may reduce respiratory drive, and the resultant CO2 retention can further increase intracranial pressure. Monitor such patients for signs of increasing intracranial pressure. Monitor such patients closely, particularly when initiating and titrating Fentanyl Citrate Injection and when Fentanyl Citrate Injection is given concomitantly with other drugs that depress respiration [see Warnings and Precautions (5.2), Drug Interactions (7)].

Opioids may also obscure the clinical course in a patient with a head injury.

5.11 Risks of Use in Patients with Gastrointestinal Conditions

Fentanyl may cause spasm of the sphincter of Oddi. Opioids may cause increases in serum amylase. Monitor patients with biliary tract disease, including acute pancreatitis, for worsening symptoms.

5.12 Increased Risk of Seizures in Patients with Seizure Disorders

Fentanyl may increase the frequency of seizures in patients with seizure disorders and may increase the risk of seizures occurring in other clinical setting associated with seizures. Monitor patients with a history of seizure disorders for worsened seizure control during Fentanyl Citrate Injection therapy.

5.13 Risks of Driving and Operating Machinery

Fentanyl Citrate Injection may impair the mental or physical abilities needed to perform potentially hazardous activities such as driving a car or operating machinery after Fentanyl Citrate Injection administration. Warn patients not to drive or operate dangerous machinery unless they are tolerant to the effects of Fentanyl Citrate Injection and know how they will react to the medication.

5.14 Risks due to Interaction with Neuroleptic Agents

Many neuroleptic agents have been associated with QT prolongation, torsades de pointes, and cardiac arrest. Administer neuroleptic agents with extreme caution in the presence of risk factors for development of prolonged QT syndrome and torsades de pointes, such as: 1) clinically significant bradycardia (less than 50 bpm), 2) any clinically significant cardiac disease, including baseline prolonged QT interval, 3) treatment with Class I and Class III antiarrhythmics, 4) treatment with monoamine oxidase inhibitors (MAOI’s), 5) concomitant treatment with other drug products known to prolong the QT interval and 6) electrolyte imbalance, in particular hypokalemia and hypomagnesemia, or concomitant treatment with drugs (e.g., diuretics) that may cause electrolyte imbalance.

Elevated blood pressure, with and without pre-existing hypertension, has been reported following administration of Fentanyl Citrate Injection combined with a neuroleptic. This might be due to unexplained alterations in sympathetic activity following large doses; however, it is also frequently attributed to anesthetic and surgical stimulation during light anesthesia.

ECG monitoring is indicated when a neuroleptic agent is used in conjunction with Fentanyl Citrate Injection as an anesthetic premedication, for the induction of anesthesia, or as an adjunct in the maintenance of general or regional anesthesia.

When Fentanyl Citrate Injection is used with a neuroleptic and an EEG is used for postoperative monitoring, the EEG pattern may return to normal slowly.

6 ADVERSE REACTIONS

The following serious adverse reactions are described, or described in greater detail, in other sections:

- Addiction, Abuse, and Misuse [see Warnings and Precautions (5.1)]
- Life-Threatening Respiratory Depression [see Warnings and Precautions (5.2)]
- Interactions with Benzodiazepines and Other CNS Depressants [see Warnings and Precautions (5.4)]
- Severe Cardiovascular Depression [see Warnings and Precautions (5.6)]
- Opioid-Induced Hyperalgesia and Allodynia [see Warnings and Precautions (5.7)]
- Serotonin Syndrome [see Warnings and Precautions (5.8)]
- Gastrointestinal Adverse Reactions [see Warnings and Precautions (5.11)]
- Seizures [see Warnings and Precautions (5.12)]

The following adverse reactions associated with the use of fentanyl were identified in clinical studies or postmarketing reports. Because some of these reactions were reported voluntarily from a population of uncertain size, it is not always possible to reliably estimate their frequency or establish a causal relationship to drug exposure.

As with other opioid agonists, the most common serious adverse reactions reported to occur with fentanyl are respiratory depression, apnea, rigidity and bradycardia; if these remain untreated, respiratory arrest, circulatory depression or cardiac arrest could occur. Other adverse reactions that have been reported are hypertension, hypotension, dizziness, blurred vision, nausea, emesis, laryngospasm, diaphoresis, serotonin syndrome, adrenal insufficiency, and anaphylaxis.

It has been reported that secondary rebound respiratory depression may occasionally occur postoperatively. When a tranquilizer is used with Fentanyl Citrate Injection, the following adverse reactions can occur: chills and/or shivering, restlessness and postoperative hallucinatory episodes (sometimes associated with transient periods of mental depression); extrapyramidal symptoms (dystonia, akathisia and oculogyric crisis) have been observed up to 24 hours postoperatively. When they occur, extrapyramidal symptoms can usually be controlled with anti-parkinson agents. Postoperative drowsiness is also frequently reported following the use of neuroleptics with fentanyl citrate.

Cases of cardiac dysrhythmias, cardiac arrest, and death have been reported following the use of fentanyl citrate with a neuroleptic agent.

Serotonin syndrome: Cases of serotonin syndrome, a potentially life-threatening condition, have been reported during concomitant use of opioids with serotonergic drugs.

Adrenal insufficiency: Cases of adrenal insufficiency have been reported with opioid use, more often following greater than one month of use.

Anaphylaxis: Anaphylaxis has been reported with ingredients contained in Fentanyl Citrate Injection

Androgen deficiency: Cases of androgen deficiency have occurred with use of opioids for an extended period of time [see Clinical Pharmacology (12.2)].

Hyperalgesia and Allodynia: Cases of hyperalgesia and allodynia have been reported with opioid therapy of any duration [see Warnings and Precautions (5.7)].

Hypoglycemia: Causes of hypoglycemia have been reported in patients taking opioids. Most reports were in patients with at least one predisposing risk factor (e.g., diabetes).

7 DRUG INTERACTIONS

Table 2 includes clinically significant drug interactions with Fentanyl Citrate Injection.

Table 2: Clinically Significant Drug Interactions with Fentanyl Citrate Injection

Inhibitors of CYP3A4
Clinical Impact: | The concomitant use of Fentanyl Citrate Injection and CYP3A4 inhibitors can increase the plasma concentration of fentanyl, resulting in increased or prolonged opioid effects, particularly when an inhibitor is added after a stable dose of Fentanyl Citrate Injection is achieved [see Warnings and Precautions (5.3)]. After stopping a CYP3A4 inhibitor, as the effects of the inhibitor decline, the fentanyl plasma concentration will decrease [see Clinical Pharmacology (12.3)], resulting in decreased opioid efficacy or a withdrawal syndrome in patients who had developed physical dependence to fentanyl.
Intervention: | If concomitant use is necessary, consider dosage reduction of Fentanyl Citrate Injection until stable drug effects are achieved [see Dosage and Administration (2.1)]. Monitor patients at frequent intervals for respiratory depression and sedation. If a CYP3A4 inhibitor is discontinued, consider increasing the Fentanyl Citrate Injection dosage until stable drug effects are achieved. Monitor for signs of opioid withdrawal.
Examples: | Macrolide antibiotics (e.g., erythromycin), azole-antifungal agents (e.g., ketoconazole), protease inhibitors (e.g., ritonavir), grapefruit juice
CYP3A4 Inducers
Clinical Impact: | The concomitant use of Fentanyl Citrate Injection and CYP3A4 inducers can decrease the plasma concentration of fentanyl [see Clinical Pharmacology (12.3)], resulting in decreased efficacy or onset of a withdrawal syndrome in patients who have developed physical dependence to fentanyl [see Warnings and Precautions (5.3)]. After stopping a CYP3A4 inducer, as the effects of the inducer decline, the fentanyl plasma concentration will increase [see Clinical Pharmacology (12.3)], which could increase or prolong both the therapeutic effects and adverse reactions and may cause serious respiratory depression.
Intervention: | If concomitant use is necessary, consider increasing the Fentanyl Citrate Injection dosage until stable drug effects are achieved. Monitor for signs of opioid withdrawal. If a CYP3A4 inducer is discontinued, consider Fentanyl Citrate Injection dosage reduction and monitor for signs of respiratory depression.
Examples: | Rifampin, carbamazepine, phenytoin
Benzodiazepines and Other Central Nervous System (CNS) Depressants
Clinical Impact: | The concomitant use of Fentanyl Citrate Injection with CNS depressants may result in decreased pulmonary artery pressure and may cause hypotension. Even small dosages of diazepam may cause cardiovascular depression when added to high dose or anesthetic dosages of Fentanyl Citrate Injection. As postoperative analgesia, concomitant use of Fentanyl Citrate Injection can increase the risk of hypotension, respiratory depression, profound sedation, coma, and death.
Intervention: | As postoperative analgesia, start with a lower dose of Fentanyl Citrate Injection and monitor patients for signs of respiratory depression, sedation, and hypotension. Fluids or other measures to counter hypotension should be available [see Warnings and Precautions (5.4)].
Examples: | Benzodiazepines and other sedatives/hypnotics, anxiolytics, barbiturates, tranquilizers, muscle relaxants, general anesthetics, antipsychotics, other opioids, alcohol.
Serotonergic Drugs
Clinical Impact: | The concomitant use of opioids with other drugs that affect the serotonergic neurotransmitter system has resulted in serotonin syndrome [see Warnings and Precautions (5.8)].
Intervention: | If concomitant use is warranted, carefully observe the patient, particularly during treatment initiation and dose adjustment. Discontinue Fentanyl Citrate Injection if serotonin syndrome is suspected.
Examples: | Selective serotonin reuptake inhibitors (SSRIs), serotonin and norepinephrine reuptake inhibitors (SNRIs), tricyclic antidepressants (TCAs), triptans, 5-HT3 receptor antagonists, drugs that effect the serotonin neurotransmitter system (e.g., mirtazapine, trazodone, tramadol), certain muscle relaxants (i.e., cyclobenzaprine, metaxalone), monoamine oxidase (MAO) inhibitors (those intended to treat psychiatric disorders and also others, such as linezolid and intravenous methylene blue).
Monoamine Oxidase Inhibitors
Clinical Impact: | MAOI interactions with opioids may manifest as serotonin syndrome [see Warnings and Precautions (5.8)] or opioid toxicity (e.g., respiratory depression, coma) [see Warnings and Precautions (5.2)].
Intervention: | The use of Fentanyl Citrate Injection is not recommended for patients taking MAOIs or within 14 days of stopping such treatment.
Examples: | Phenelzine, tranylcypromine, linezolid
Mixed Agonist/Antagonist and Partial Agonist Opioid Analgesics
Clinical Impact: | May reduce the analgesic effect of Fentanyl Citrate Injection and/or precipitate withdrawal symptoms.
Intervention: | Avoid concomitant use.
Examples: | Butorphanol, nalbuphine, pentazocine, buprenorphine.
Muscle Relaxants
Clinical Impact: | Fentanyl may enhance the neuromuscular blocking action of skeletal muscle relaxants and produce an increased degree of respiratory depression.
Intervention: | Monitor patients for signs of respiratory depression that may be greater than otherwise expected and decrease the dosage of Fentanyl Citrate Injection and/or the muscle relaxant as necessary.
Diuretics
Clinical Impact: | Opioids can reduce the efficacy of diuretics by inducing the release of antidiuretic hormone.
Intervention: | Monitor patients for signs of diminished diuresis and/or effects on blood pressure and increase the dosage of the diuretic as needed.
Anticholinergic Drugs
Clinical Impact: | The concomitant use of anticholinergic drugs may increase risk of urinary retention and/or severe constipation, which may lead to paralytic ileus.
Intervention: | Monitor patients for signs of urinary retention or reduced gastric motility when Fentanyl Citrate Injection is used concomitantly with anticholinergic drugs.
Neuroleptics
Clinical Impact: | Elevated blood pressure, with and without pre-existing hypertension, has been reported following administration of Fentanyl Citrate Injection combined with a neuroleptic [see Warnings and Precautions (5.14)].
Intervention: | ECG monitoring is indicated when a neuroleptic agent is used in conjunction with Fentanyl Citrate Injection as an anesthetic premedication, for the induction of anesthesia, or as an adjunct in the maintenance of general or regional anesthesia.
Nitrous oxide
Clinical Impact: | Nitrous oxide has been reported to produce cardiovascular depression when given with higher doses of Fentanyl Citrate Injection.
Intervention: | Monitor patients for signs of cardiovascular depression that may be greater than otherwise expected.

8 USE IN SPECIFIC POPULATIONS

8.1 Pregnancy

Risk Summary

Use of opioid analgesics for an extended period of time during pregnancy may cause neonatal opioid withdrawal syndrome. Available data with Fentanyl Citrate Injection in pregnant women are insufficient to inform a drug-associated risk for major birth defects and miscarriage or adverse maternal outcomes. There are adverse outcomes reported with fetal exposure to opioid analgesics (see Clinical Considerations). In animal reproduction studies, fentanyl administration to pregnant rats during organogenesis was embryocidal at doses within the range of the human recommended dosing. No evidence of malformations was noted in animal studies completed to date [see Data].

The background risk of major birth defects and miscarriage for the indicated population is unknown. All pregnancies have a background risk of birth defect, loss, or other adverse outcomes. In the U.S. general population, the estimated background risk of major birth defects and miscarriage in clinically recognized pregnancies is 2 to 4% and 15 to 20%, respectively.

Clinical Considerations

Fetal/Neonatal Adverse Reactions

Use of opioid analgesics for an extended period of time during pregnancy for medical or nonmedical purposes can result in physical dependence in the neonate and neonatal opioid withdrawal syndrome shortly after birth.
Neonatal opioid withdrawal syndrome presents as irritability, hyperactivity and abnormal sleep pattern, high pitched cry, tremor, vomiting, diarrhea and failure to gain weight. The onset, duration, and severity of neonatal opioid withdrawal syndrome vary based on the specific opioid used, duration of use, timing and amount of last maternal use, and rate of elimination of the drug by the newborn. Observe newborns for symptoms of neonatal opioid withdrawal syndrome and manage accordingly.

Labor or Delivery

There are insufficient data to support the use of fentanyl in labor or delivery. Therefore, such use is not recommended. Opioids cross the placenta and may produce respiratory depression and psycho-physiologic effects in neonates. An opioid antagonist, such as naloxone, must be available for reversal of opioid-induced respiratory depression in the neonate. Fentanyl Citrate Injection is not recommended for use in pregnant women during or immediately prior to labor, when other analgesic techniques are more appropriate. Opioid analgesics, including Fentanyl Citrate Injection, can prolong labor through actions which temporarily reduce the strength, duration, and frequency of uterine contractions. However, this effect is not consistent and may be offset by an increased rate of cervical dilation, which tends to shorten labor. Monitor neonates exposed to opioid analgesics during labor for signs of excess sedation and respiratory depression.

Data

Animal Data

Fentanyl has been shown to be embryocidal in pregnant rats at doses of 30 mcg/kg intravenously (0.05 times the human dose of 100 mcg/kg on a mg/m^2 basis) and 160 mcg/kg subcutaneously (0.26 times the human dose of 100 mcg/kg on a mg/m^2 basis). There was no evidence of teratogenicity reported.
No evidence of malformations or adverse effects on the fetus was reported in a published study in which pregnant rats were administered fentanyl continuously via subcutaneously implanted osmotic minipumps at doses of 10, 100, or 500 mcg/kg/day starting 2-weeks prior to breeding and throughout pregnancy. The high dose was approximately 0.81 times the human dose of 100 mcg/kg on a mg/m^2 basis.

8.2 Lactation

Risk Summary

Fentanyl is present in breast milk. One published lactation study reports a relative infant dose of fentanyl of 0.38%. However, there is insufficient information to determine the effects of fentanyl on the breastfed infant and the effects of fentanyl on milk production. The developmental and health benefits of breastfeeding should be considered along with the mother’s clinical need for Fentanyl Citrate Injection and any potential adverse effects on the breastfed infant from Fentanyl Citrate Injection or from the underlying maternal condition.

Clinical Considerations

Monitor infants exposed to fentanyl through breast milk for excess sedation and respiratory depression. Withdrawal symptoms can occur in breastfed infants when maternal administration of an opioid analgesic is stopped, or when breast-feeding is stopped.

8.3 Females and Males of Reproductive Potential

Infertility

Use of opioids for an extended period of time may cause reduced fertility in females and males of reproductive potential. It is not known whether these effects on fertility are reversible [see Adverse Reactions (6), Clinical Pharmacology (12.2), Nonclinical Toxicology (13.1)].

8.4 Pediatric Use

The safety and efficacy of Fentanyl Citrate Injection in pediatric patients under two years of age has not been established.

Rare cases of unexplained clinically significant methemoglobinemia have been reported in premature neonates undergoing emergency anesthesia and surgery which included combined use of fentanyl, pancuronium and atropine. A direct cause and effect relationship between the combined use of these drugs and the reported cases of methemoglobinemia has not been established.

8.5 Geriatric Use

Elderly patients (aged 65 years or older) may have increased sensitivity to fentanyl. In general, use caution when selecting a dosage for an elderly patient, usually starting at the low end of the dosing range, reflecting the greater frequency of decreased hepatic, renal, or cardiac function and of concomitant disease or other drug therapy.

Respiratory depression is the chief risk for elderly patients treated with opioids, and has occurred after large initial doses were administered to patients who were not opioid-tolerant or when opioids were co-administered with other agents that depress respiration. Titrate the dosage of Fentanyl Citrate Injection slowly in geriatric patients and monitor closely for signs of central nervous system and respiratory depression [see Warnings and Precautions (5.2)].

Fentanyl is known to be substantially excreted by the kidney, and the risk of adverse reactions to this drug may be greater in patients with impaired renal function. Because elderly patients are more likely to have decreased renal function, care should be taken in dose selection, and it may be useful to monitor renal function.

8.6 Hepatic Impairment

Fentanyl Citrate Injection should be administered with caution to patients with liver dysfunction because of the extensive hepatic metabolism. Reduce the dosage as needed and monitor closely for signs of respiratory depression, sedation, and hypotension.

8.7 Renal Impairment

Fentanyl Citrate Injection should be administered with caution to patients with kidney dysfunction because of the renal excretion of Fentanyl Citrate Injection and its metabolites. Reduce the dosage as needed and monitor closely for signs of respiratory depression, sedation, and hypotension.

9 DRUG ABUSE AND DEPENDENCE

9.1 Controlled Substance

Fentanyl Citrate Injection contains fentanyl, a Schedule II controlled drug substance.

9.2 Abuse

Fentanyl Citrate Injection contains fentanyl, a substance with a high potential for misuse and abuse, which can lead to the development of substance use disorder, including addiction [see Warnings and Precautions (5.1)].

Misuse is the intentional use, for therapeutic purposes, of a drug by an individual in a way other than prescribed by healthcare provider or for whom it was not prescribed.

Abuse is the intentional, non-therapeutic use of a drug, even once, for its desirable psychological or physiological effects.

Drug addiction is a cluster of behavioral, cognitive, and physiological phenomena that may include a strong desire to take the drug, difficulties in controlling drug use (e.g., continuing drug use despite harmful consequences, giving a higher priority to drug use than other activities and obligations), and possible tolerance or physical dependence.
Misuse and abuse of Fentanyl Citrate Injection increases risk of overdose, which may lead to central nervous system and respiratory depression, hypotension, seizures, and death. The risk is increased with concurrent abuse of Fentanyl Citrate Injection with alcohol and/or other CNS depressants. Abuse of and addiction to opioids in some individuals may not be accompanied by concurrent tolerance and symptoms of physical dependence. In addition, abuse of opioids can occur in the absence of addiction.

All patients treated with opioids require careful and frequent reevaluation for signs of misuse, abuse, and addiction, because use of opioid analgesic products carries the risk of addiction even under appropriate medical use. Patients at high risk of Fentanyl Citrate Injection abuse include those with a history of prolonged use of any opioid, including products containing fentanyl, those with a history of drug or alcohol abuse, or those who use Fentanyl Citrate Injection in combination with other abused drugs.

“Drug-seeking” behavior is very common in persons with substance use disorders. Drug-seeking tactics include emergency calls or visits near the end of office hours, refusal to undergo appropriate examination, testing or referral, repeated “loss” of prescriptions, tampering with prescriptions, and reluctance to provide prior medical records or contact information for other treating healthcare providers(s). “Doctor shopping” (visiting multiple prescribers to obtain additional prescriptions) is common among people who abuse drugs and people with substance use disorder. Preoccupation with achieving adequate pain relief can be appropriate behavior in a patient with inadequate pain control.

Fentanyl Citrate Injection, like other opioids, can be diverted for nonmedical use into illicit channels of distribution. Careful record-keeping of prescribing information, including quantity, frequency, and renewal requests, as required by state and federal law, is strongly advised.

Proper assessment of the patient, proper prescribing practices, periodic reevaluation of therapy, and proper dispensing and storage are appropriate measures to limit abuse of opioid drugs.

Risks Specific to Abuse of Fentanyl Citrate Injection

Abuse of Fentanyl Citrate Injection poses a risk of overdose and death. The risk is increased with concurrent use of Fentanyl Citrate Injection with alcohol and/or other CNS depressants.

Parenteral drug abuse is commonly associated with transmission of infectious diseases such as hepatitis and HIV.

9.3 Dependence

Both tolerance and physical dependence can develop during chronic opioid therapy.
Tolerance is a physiological state characterized by a reduced response to a drug after repeated administration (i.e., a higher dose of a drug is required to produce the same effect that was once obtained at a lower dose).

Physical dependence is a state that develops as a result of physiological adaptation in a response to repeated drug use, manifested by withdrawal signs and symptoms after abrupt discontinuation or a significant dosage reduction of a drug.

Withdrawal also may be precipitated through the administration of drugs with opioid antagonist activity (e.g., naloxone), mixed agonist/antagonist analgesics (e.g., pentazocine, butorphanol, nalbuphine), or partial agonists (e.g., buprenorphine). Physical dependence may not occur to a clinically significant degree until after several days to weeks of continued use.

Fentanyl Citrate Injection should not be abruptly discontinued in a physically-dependent patient. If Fentanyl Citrate Injection is abruptly discontinued in a physically-dependent patient, a withdrawal syndrome may occur, typically characterized by restlessness, lacrimation, rhinorrhea, perspiration, chills, myalgia, and mydriasis. Other signs and symptoms also may develop, including irritability, anxiety, backache, joint pain, weakness, abdominal cramps, insomnia, nausea, anorexia, vomiting, diarrhea, or increased blood pressure, respiratory rate, or heart rate.

Infants born to mothers physically dependent on opioids will also be physically dependent and may exhibit respiratory difficulties and withdrawal signs [see Use in Specific Populations (8.1)].

10 OVERDOSAGE

Clinical Presentation

Acute overdose with fentanyl can be manifested by respiratory depression, somnolence progressing to stupor or coma, skeletal muscle flaccidity, cold and clammy skin, constricted pupils, and, in some cases, pulmonary edema, bradycardia, hypotension, hypoglycemia, partial or complete airway obstruction, atypical snoring, and death. Marked mydriasis rather than miosis may be seen with hypoxia in overdose situations [see Clinical Pharmacology (12.2)].

Treatment of Overdose

In case of overdose, priorities are the reestablishment of a patent and protected airway and institution of assisted or controlled ventilation, if needed. Employ other supportive measures (including oxygen and vasopressors) in the management of circulatory shock and pulmonary edema as indicated. Cardiac arrest or arrhythmias will require advanced life-support measures.
Opioid antagonists, such as naloxone, are specific antidotes to respiratory depression resulting from opioid overdose. For clinically significant respiratory or circulatory depression secondary to fentanyl overdose, administer an opioid antagonist.
Because the duration of opioid reversal is expected to be less than the duration of action of fentanyl in Fentanyl Citrate Injection, carefully monitor the patient until spontaneous respiration is reliably re-established. If the response to an opioid antagonist is suboptimal or only brief in nature, administer additional antagonist as directed by the product’s prescribing information.
In an individual physically dependent on opioids, administration of the recommended usual dosage of the antagonist will precipitate an acute withdrawal syndrome. The severity of the withdrawal symptoms experienced will depend on the degree of physical dependence and the dose of the antagonist administered. If a decision is made to treat serious respiratory depression in the physically dependent patient, administration of the antagonist should be initiated with care and by titration with smaller than usual doses of the antagonist.

11 DESCRIPTION

Fentanyl Citrate Injection is an opioid agonist, available as a sterile, non-pyrogenic solution containing fentanyl citrate as the active pharmaceutical ingredient, for intravenous or intramuscular administration.
Fentanyl citrate is chemically identified as N-(1-Phenethyl-4-piperidyl)propionanilide citrate (1:1) with the following structural formula:

C22H28N2O • C6H8O7 Molecular Weight is 528.59

Each mL contains fentanyl citrate equivalent to 50 mcg fentanyl base in Water for Injection. Sodium hydroxide and/or hydrochloric acid added, if needed, for pH adjustment. The pH range is 4.0 – 7.5. Contains no preservative.

12 CLINICAL PHARMACOLOGY

12.1 Mechanism of Action

Fentanyl Citrate Injection is an opioid agonist, whose principal actions of therapeutic value are analgesia and sedation.

12.2 Pharmacodynamics

Effects on the Central Nervous System

Fentanyl produces respiratory depression by direct action on brain stem respiratory centers. The respiratory depression involves a reduction in the responsiveness of the brain stem respiratory centers to both increases in carbon dioxide tension and electrical stimulation. Fentanyl causes miosis, even in total darkness. Pinpoint pupils are a sign of opioid overdose but are not pathognomic (e.g., pontine lesions of hemorrhagic or ischemic origins may produce similar findings). Marked mydriasis rather than miosis may be seen due to hypoxia in overdose situations.

Effects on the Gastrointestinal Tract and Other Smooth Muscle

Fentanyl causes a reduction in motility associated with an increase in smooth muscle tone in the antrum of the stomach and duodenum. Digestion of food in the small intestine is delayed and propulsive contractions are decreased. Propulsive peristaltic waves in the colon are decreased, while tone may be increased to the point of spasm, resulting in constipation. Other opioid-induced effects may include a reduction in biliary and pancreatic secretions, spasm of sphincter of Oddi, and transient elevations in serum amylase.

Effects on the Cardiovascular System

Fentanyl produces peripheral vasodilation which may result in orthostatic hypotension or syncope. Manifestations of histamine release and/or peripheral vasodilation may include pruritis, flushing, red eyes, sweating, and/or orthostatic hypotension.

Effects on the Endocrine System

Opioids inhibit the secretion of adrenocorticotropic hormone (ACTH), cortisol, and lutenizing hormone (LH) in humans [see Adverse Reactions (6)]. They also stimulate prolactin, growth hormone (GH) secretion, and pancreatic secretion of insulin and glucagon.
Use of opioids for an extended period of time may influence the hypothalamic-pituitary-gonadal axis, leading to androgen deficiency that may manifest as low libido, impotence, erectile dysfunction, amenorrhea, or infertility. The causal role of opioids in the clinical syndrome of hypogonadism is unknown because the various medical, physical, lifestyle, and psychological stressors that may influence gonadal hormone levels have not been adequately controlled for in studies conducted to date [see Adverse Reactions (6)].

Effects on the Immune System

Opioids have been shown to have a variety of effects on components of the immune system in in vitro and animal models. The clinical significance of these findings is unknown. Overall, the effects of opioids appear to be modestly immunosuppressive.

Concentration – Efficacy Relationships

A dose of 100 mcg of Fentanyl Citrate Injection is approximately equivalent in analgesic activity to 10 mg of morphine or 75 mg of meperidine.
The minimum effective analgesic concentration will vary widely among patients, especially among patients who have been previously treated with opioid agonists. The minimum effective analgesic concentration of fentanyl for any individual patient may increase over time due to an increase in pain, the development of a new pain syndrome and/or the development of analgesic tolerance [see Dosage and Administration (2.1)].
The onset of action of fentanyl is almost immediate when the drug is given intravenously; however, the maximal analgesic effect may not be noted for several minutes. The usual duration of action of the analgesic effect is 30 to 60 minutes after a single intravenous dose of up to 100 mcg. Following intramuscular administration, the onset of action is from seven to eight minutes, and the duration of action is one to two hours.

Concentration – Adverse Reaction Relationships

There is a relationship between increasing fentanyl plasma concentration and increasing frequency of dose-related opioid adverse reactions such as nausea, vomiting, CNS effects, and respiratory depression. In opioid-tolerant patients, the situation may be altered by the development of tolerance to opioid-related adverse reactions [see Dosage and Administration (2.1)].
The onset of action of fentanyl is almost immediate when the drug is given intravenously; however, the maximal respiratory depressant effect may not be noted for several minutes. As with longer acting narcotic analgesics, the duration of the respiratory depressant effect of fentanyl may be longer than the analgesic effect. The following observations have been reported concerning altered respiratory response to CO2 stimulation following administration of fentanyl citrate:

- Diminished sensitivity to CO2 stimulation may persist longer than depression of respiratory rate. (Altered sensitivity to CO2 stimulation has been demonstrated for up to four hours following a single dose of 600 mcg fentanyl to healthy volunteers.) Fentanyl frequently slows the respiratory rate, duration and degree of respiratory depression being dose related.
- The peak respiratory depressant effect of a single intravenous dose of fentanyl citrate is noted 5 to 15 minutes following injection [see Warnings and Precautions (5.2)].

12.3 Pharmacokinetics

Fentanyl Citrate Injection is administered by the intravenous or intramuscular route. The pharmacokinetics of fentanyl can be described as a three-compartment model.

Distribution

Fentanyl plasma protein binding capacity increases with increasing ionization of the drug. Alterations in pH may affect its distribution between plasma and the central nervous system. It accumulates in skeletal muscle and fat and is released slowly into the blood. The volume of distribution for fentanyl is 4 L/kg. It has a distribution time of 1.7 minutes and redistribution time of 13 minutes.

Elimination

The terminal elimination half-life is 219 minutes.
Fentanyl, which is primarily transformed in the liver, demonstrates a high first pass clearance and releases approximately 75% of an intravenous dose in urine, mostly as metabolites with less than 10% representing the unchanged drug. Approximately 9% of the dose is recovered in the feces, primarily as metabolites.

13 NONCLINICAL TOXICOLOGY

13.1 Carcinogenesis, Mutagenesis, Impairment of Fertility

Carcinogenesis

Long-term studies in animals to evaluate the carcinogenic potential of fentanyl citrate have not been conducted.

Mutagenesis

No formal studies to assess the mutagenic potential of fentanyl citrate have been conducted.

Impairment of Fertility

Decreased pregnancy rates occurred in a multigenerational study in which pregnant rats were treated subcutaneously during the first 21 days of pregnancy with 160 mcg/kg to 1250 mcg/kg fentanyl (0.26 times to 2.0 times a human dose of 100 mcg/kg based on body surface area).

Studies in animals to characterize the effect of fentanyl on male fertility have not been conducted.

16 HOW SUPPLIED/STORAGE AND HANDLING

Fentanyl Citrate Injection, equivalent to 50 mcg fentanyl base per mL, is a preservative-free solution, supplied as follows:

NDC 81565-205-02 2 mL Single Dose vials packaged in 25s

PROTECT FROM LIGHT. Keep covered in carton until time of use. Store at 20˚C to 25˚C (68˚F to 77˚F), excursions permitted to 15˚C to 30˚C (59˚F to 86˚F) [See USP Controlled Room Temperature]. Contains no preservative. DISCARD ANY UNUSED CONTENTS.

Parenteral drug products should be inspected visually for particulate matter and discoloration prior to administration, whenever solution and container permit.

To report SUSPECTED ADVERSE REACTIONS, contact Hikma Pharmaceuticals USA Inc. at 1-877-845-0689, or the FDA at 1-800-FDA-1088 or www.fda.gov/medwatch.

For Product Inquiry call 1-877-845-0689.

17 PATIENT COUNSELING INFORMATION

Addiction, Abuse, and Misuse

Inform patients that the use of Fentanyl Citrate Injection, even when taken as recommended, can result in addiction, abuse, and misuse, which can lead to overdose and death [see Warnings and Precautions (5.1)].

Life-Threatening Respiratory Depression

Inform patients of the risk of life-threatening respiratory depression, including information that the risk is greatest when starting Fentanyl Citrate Injection or when the dosage is increased, and that it can occur even at recommended dosages.

Hyperalgesia and Allodynia

Advise patients to inform their healthcare provider if they experience symptoms of hyperalgesia, including worsening pain, increased sensitivity to pain, or new pain [see Warnings and Precautions (5.7); Adverse Reactions (6)].

Serotonin Syndrome

Inform patients that opioids could cause a rare but potentially life-threatening condition called serotonin syndrome resulting from concomitant administration of serotonergic drugs. Warn patients of the symptoms of serotonin syndrome and to seek medical attention right away if symptoms develop after discharge from the hospital. Instruct patients to inform their healthcare provider if they are taking, or plan to take serotonergic medications [see Warnings and Precautions (5.8), Drug Interactions (7)].

Constipation

Advise patients of the potential for severe constipation, including management instructions and when to seek medical attention [see Clinical Pharmacology (12.2)].

Distributed by:

Phlow Corporation
Richmond, VA 23224

Manufactured by:

Hikma Pharmaceuticals USA Inc.
Berkeley Heights, NJ 07922

Revised: December 2023

462-958-02

PRINCIPAL DISPLAY PANEL

Rx only

2 mL Single Dose

NDC 81565-205-01

Fentanyl Citrate Inj., USP CII

100 mcg per 2 mL

(50 mcg/mL)

FOR IV OR IM USE

Protect from light

Discard unused portion

Rx only

NDC 81565-205-02

Fentanyl Citrate Injection, USP CII

100 mcg per 2 mL

(50 mcg/mL)

For Intravenous or Intramuscular use

Preservative-free

25 x 2 mL Single Dose Vials